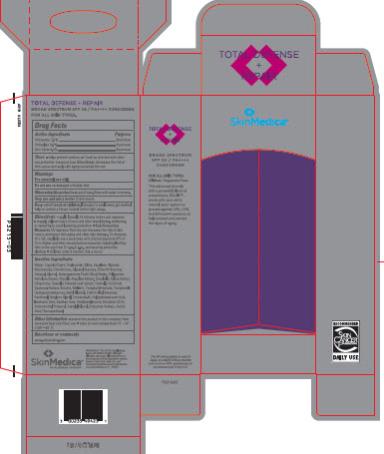 DRUG LABEL: TOTAL DEFENSE REPAIR BROAD SPECTRUM SPF 34 Sunscreen
NDC: 0023-5494 | Form: LOTION
Manufacturer: Allergan, Inc.
Category: otc | Type: HUMAN OTC DRUG LABEL
Date: 20150901

ACTIVE INGREDIENTS: OCTINOXATE 75 mg/1 g; OCTISALATE 30 mg/1 g; ZINC OXIDE 80 mg/1 g
INACTIVE INGREDIENTS: WATER; MEDIUM-CHAIN TRIGLYCERIDES; SILICON DIOXIDE; SQUALANE; GLYCERIN; NIACINAMIDE; DIMETHICONE, UNSPECIFIED; GLYCERYL MONOSTEARATE; PEG-100 MONOSTEARATE; CETOSTEARYL ALCOHOL; SHEA BUTTER; POLYGONUM AVICULARE TOP; PHYSALIS ANGULATA WHOLE; DUNALIELLA SALINA; UBIDECARENONE; GREEN TEA LEAF; TREMELLA FUCIFORMIS FRUITING BODY; BETAINE; MELANIN SYNTHETIC (TYROSINE, PEROXIDE); ALPHA-TOCOPHEROL ACETATE; TOCOPHEROL; HYDROXYACETOPHENONE; BATILOL; ALKYL (C12-15) BENZOATE; PANTHENOL; BUTYLENE GLYCOL; POLYOXYL 20 CETOSTEARYL ETHER; POLYHYDROXYSTEARIC ACID (2300 MW); ISOSTEARIC ACID; XANTHAN GUM; ETHYLHEXYLGLYCERIN; EDETATE DISODIUM ANHYDROUS; AMINOMETHYLPROPANOL; CAPRYLYL GLYCOL; POTASSIUM SORBATE; SORBIC ACID; PHENOXYETHANOL

TOTAL DEFENSE REPAIR BROAD SPECTRUM SPF 34 SUNSCREEN- octinoxate, octisalate and zinc oxide lotion
Allergan, Inc.
Total Defense Repair Broad Spectrum SPF 34 Sunscreen
Drug Facts

Active ingredients

Octinoxate 7.5%

Octisalate 3.0%

Zinc Oxide 8.0%

Purpose

Sunscreen

Sunscreen

Sunscreen

Uses

- helps prevent sunburn
- if used as directed with other sun protection measures (see Directions), decreases the risk of skin cancer and early skin aging caused by the sun

Warnings

For external use only

Do not use

on damaged or broken skin

When using this product

keep out of eyes. Rinse with water to remove.

Stop use and ask a doctor

if rash occurs

Keep out of reach of children.

If product is swallowed, get medical help or contact a Poison Control Center right away.

Directions

- apply liberally 15 minutes before sun exposure
- reapply at least every 2 hours and after towel drying, swimming, or sweating to avoid lowering protection
- Sun Protection Measures UV exposure from the sun increases the risk of skin cancer, premature skin aging and other skin damage. To decrease this risk, regularly use a sunscreen with a broad spectrum SPF of 15 or higher and other sun protection measures including limiting time in the sun from 10 a.m.-2 p.m., and wearing protective clothing
- children under 6 months: Ask a doctor

Inactive ingredients

Water, Caprylic/Capric Triglyceride, Silica, Squalane, Glycerin, Niacinamide, Dimethicone, Glyceryl Stearate, PEG-100 Stearate, Cetearyl Alcohol, Butyrospermum Parkii (Shea) Butter, Polygonum Aviculare Extract, Physalis Angulata Extract, Dunaliella Salina Extract, Ubiquinone, Camellia Sinensis Leaf Extract, Tremella Fuciformis Sporocarp Extract, Betaine, Melanin, Tocopheryl Acetate, Tocopherol, Hydroxyacetophenone, Batyl Alcohol, C12-15 Alkyl Benzoate, Panthenol, Butylene Glycol, Ceteareth-20, Polyhydroxystearic Acid, Isostearic Acid, Xanthan Gum, Ethylhexylglycerin, Disodium EDTA, Aminomethyl Propanol, Caprylyl Glycol, Potassium Sorbate, Sorbic Acid, Phenoxyethanol

Other information

- protect the product in this container from excessive heat and direct sun
- store at room temperature 15°- 30°C (59°- 86°F)

Questions or comments

www.skinmedica.com

Principal Display Panel - Carton Label

NDC 0023-5494-23

TOTAL DEFENSE
+
REPAIR
BROAD SPECTRUM
SPF 34 / PA++++
SUNSCREEN
Net Wt. 2.3 Oz. / 65 g